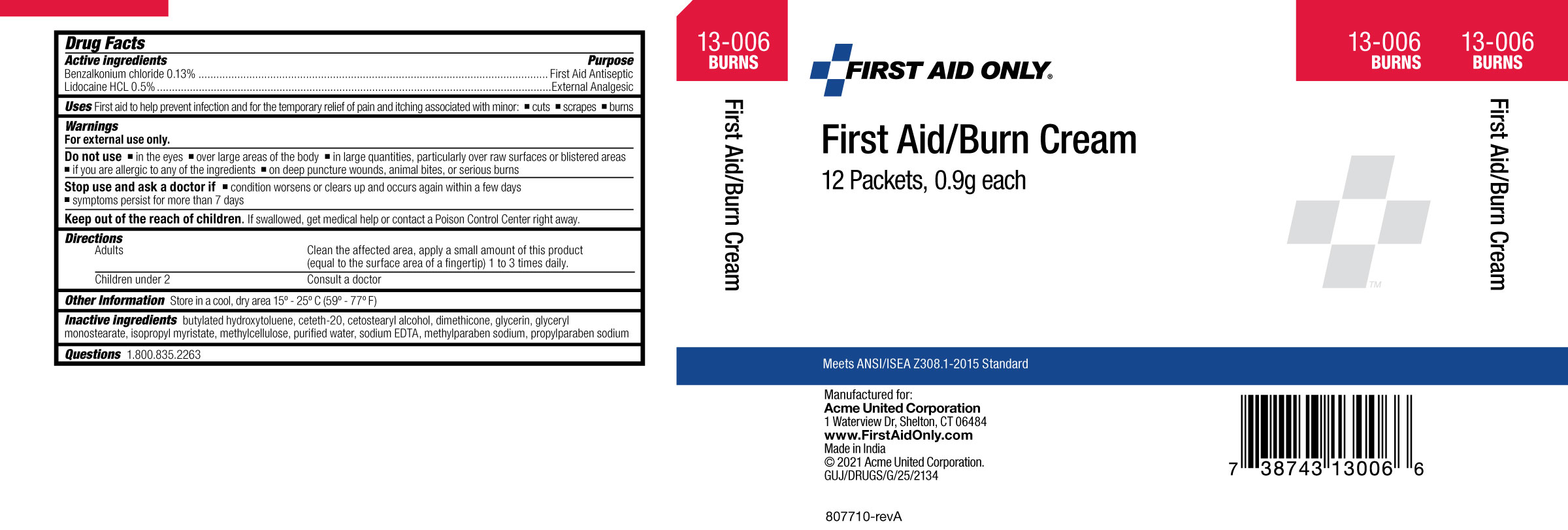 DRUG LABEL: First Aid Only First Aid/Burn
NDC: 0924-5011 | Form: CREAM
Manufacturer: Acme United Corporation
Category: otc | Type: HUMAN OTC DRUG LABEL
Date: 20241117

ACTIVE INGREDIENTS: LIDOCAINE HYDROCHLORIDE 5 mg/1 g; BENZALKONIUM CHLORIDE 1.3 mg/1 g
INACTIVE INGREDIENTS: BUTYLATED HYDROXYTOLUENE; CETETH-20; CETOSTEARYL ALCOHOL; DIMETHICONE; GLYCERIN; GLYCERYL MONOSTEARATE; ISOPROPYL MYRISTATE; METHYLCELLULOSE (25 MPA.S); WATER; EDETATE SODIUM; METHYLPARABEN SODIUM; PROPYLPARABEN SODIUM

First Aid Only First Aid/Burn Cream

Drug Facts

ACTIVE INGREDIENTS

Benzalkonium Chloride 0.13%

Lidocaine HCl 0.5%

PURPOSE

First Aid Antiseptic

External analgesic

USES

First aid to help prevent infection and for the temporary relief of pain and itching associated with minor: •cuts •scrapes •burns.

WARNINGS

For external use only.

Do not use ▪in the eyes ▪over large areas of the body ▪in large quantities, particularly over raw surfaces or blistered areas ▪if you are allergic to any of the ingredients ▪on deep puncture wounds, animal bites, or serious burns

- Stop use and ask a doctor if ▪condition worsens or clears up and occurs again within a few days ▪symptoms persist for more than 7 days ▪a rash or allergic reaction occurs

Keep out of reach of children.

If swallowed, get medical help or contact a Poison Control Center right away.

DIRECTIONS

Adults - Clean the affected area, apply a small amount of product (equal to the surface area of a fingertip) 1 to 3 times daily.

Children under 2- Consult a doctor

OTHER INFORMATION

Store in a cool dry area 150 – 250C (590 – 770F)

INACTIVE INGREDIENTS

butylated hydroxytoluene, ceteth-20, cetostearyl alcohol, dimethicone, glycerin, glyceryl monostearate, isopropyl myristate, methylcellulose, purified water, sodium EDTA, methyl paraben sodium, propylparaben sodium

Questions 1.800.835.2263

carton label